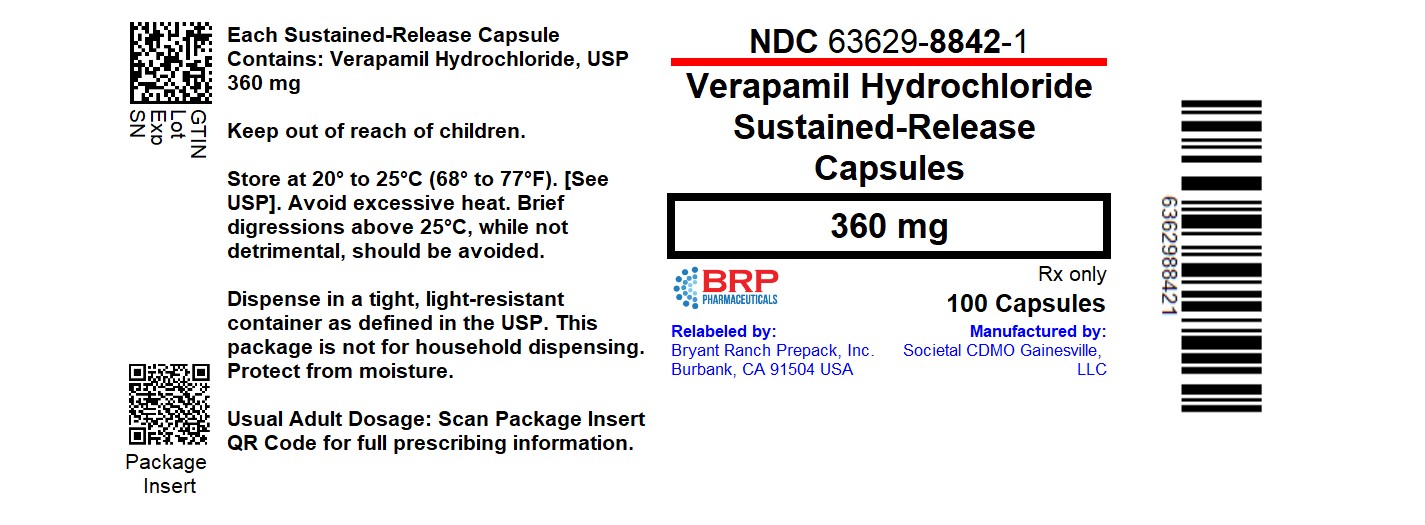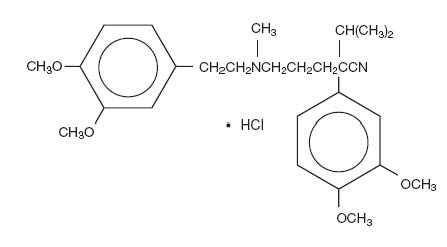 DRUG LABEL: Verapamil Hydrochloride
NDC: 63629-8842 | Form: CAPSULE, DELAYED RELEASE PELLETS
Manufacturer: Bryant Ranch Prepack
Category: prescription | Type: HUMAN PRESCRIPTION DRUG LABEL
Date: 20251117

ACTIVE INGREDIENTS: VERAPAMIL HYDROCHLORIDE 360 mg/1 1
INACTIVE INGREDIENTS: FUMARIC ACID; TALC; SUCROSE; STARCH, CORN; POVIDONE, UNSPECIFIED; SHELLAC; GELATIN, UNSPECIFIED; FD&C RED NO. 40; FERRIC OXIDE YELLOW; TITANIUM DIOXIDE; METHYLPARABEN; PROPYLPARABEN; SILICON DIOXIDE; SODIUM LAURYL SULFATE; FD&C BLUE NO. 1; D&C RED NO. 28

Verapamil Hydrochloride
Sustained-Release Capsules

Rx only

DESCRIPTION

Verapamil hydrochloride sustained-release capsules are calcium ion influx inhibitors (slow channel blockers or calcium ion antagonists). Verapamil hydrochloride sustained-release capsules are available for oral administration as a 360 mg hard gelatin capsule (lavender cap/yellow body), a 240 mg hard gelatin capsule (dark blue cap/yellow body), a 180 mg hard gelatin capsule (light grey cap/yellow body), and a 120 mg hard gelatin capsule (yellow cap/yellow body). These pellet-filled capsules provide a sustained-release of the drug in the gastrointestinal tract.

The structural formula of verapamil HCl is given below:
C27H38N2O4•HCl M.W. 491.07

Chemical name: Benzeneacetonitrile, α-[3-[[2-(3,4-dimethoxyphenyl)-ethyl]methylamino]propyl]-3,4-dimethoxy-α-(1-methylethyl), monohydrochloride.

Verapamil HCl is an almost white, crystalline powder, practically free of odor, with a bitter taste. It is soluble in water, chloroform and methanol. Verapamil HCl is not structurally related to other cardioactive drugs.

In addition to verapamil HCl the verapamil hydrochloride sustained-release capsules contain the following inactive ingredients: fumaric acid, talc, sugar spheres, povidone, shellac, gelatin, FD&C red #40, yellow iron oxide, titanium dioxide, methylparaben, propylparaben, silicon dioxide, and sodium lauryl sulfate. In addition, the verapamil hydrochloride sustained-release capsules 240 mg and 360 mg capsules contain FD&C blue #1 and D&C red #28; and the verapamil hydrochloride sustained-release capsules 180 mg contain black iron oxide.

CLINICAL PHARMACOLOGY

Verapamil hydrochloride sustained-release capsules are a calcium ion influx inhibitor (slow channel blockers or calcium ion antagonists) which exerts its pharmacologic effects by modulating the influx of ionic calcium across the cell membrane of the arterial smooth muscle as well as in conductile and contractile myocardial cells.

Normal sinus rhythm is usually not affected by verapamil HCl. However in patients with sick sinus syndrome, verapamil HCl may interfere with sinus node impulse generation and may induce sinus arrest or sinoatrial block. Atrioventricular block can occur in patients without preexisting conduction defects. (See WARNINGS.) Verapamil HCl does not alter the normal atrial action potential or intraventricular conduction time, but depresses amplitude, velocity of depolarization and conduction in depressed atrial fibers. Verapamil HCl may shorten the antegrade effective refractory period of accessory bypass tracts. Acceleration of ventricular rate and/or ventricular fibrillation has been reported in patients with atrial flutter or atrial fibrillation and a coexisting accessory AV pathway following administration of verapamil. (See WARNINGS.)

Verapamil HCl has a local anesthetic action that is 1.6 times that of procaine on an equimolar basis. It is not known whether this action is important at the doses used in man.

Mechanism of Action

Essential Hypertension
Verapamil HCl exerts antihypertensive effects by decreasing systemic vascular resistance, usually without orthostatic decreases in blood pressure or reflex tachycardia; bradycardia (rate less than 50 beats/minute is uncommon). Verapamil HCl regularly reduces arterial pressure at rest and at a given level of exercise by dilating peripheral arterioles and reducing the total peripheral resistance (afterload) against which the heart works.

Pharmacokinetics and Metabolism

With the immediate release formulations, more than 90% of the orally administered dose is absorbed, and peak plasma concentrations of verapamil are observed 1 to 2 hours after dosing. Because of rapid biotransformation of verapamil during its first pass through the portal circulation, the absolute bioavailability ranges from 20% to 35%. Chronic oral administration of the highest recommended dose (120 mg every 6 hours) resulted in plasma verapamil levels ranging from 125 to 400 ng/mL with higher values reported occasionally. A nonlinear correlation between the verapamil HCl dose administered and verapamil plasma levels does exist.

During initial dose titration with verapamil a relationship exists between verapamil plasma concentrations and the prolongation of the PR interval. However, during chronic administration this relationship may disappear. The quantitative relationship between plasma verapamil concentrations and blood pressure reduction has not been fully characterized.

In a multiple dose pharmacokinetic study, peak concentrations for a single daily dose of verapamil hydrochloride sustained-release capsules 240 mg were approximately 65% of those obtained with an 80 mg t.i.d. dose of the conventional immediate-release tablets, and the 24 hour post-dose concentrations were approximately 30% higher. At a total daily dose of 240 mg, verapamil hydrochloride sustained-release capsules was shown to have a similar extent of verapamil bioavailability based on the AUC-24 as that obtained with the conventional immediate-release tablets. In this same study verapamil hydrochloride sustained-release capsules doses of 120 mg, 240 mg and 360 mg once daily were compared after multiple doses. The ratios of the verapamil and norverapamil AUCs for the verapamil hydrochloride sustained-release capsules 120 mg, 240 mg and 360 mg once daily doses are 1 (565 ng∙hr/mL):3 (1660 ng∙hr/mL):5 (2729 ng∙hr/mL) and 1 (621 ng∙hr/mL):3 (1614 ng∙ hr/mL):4 (2535 ng∙hr/mL) respectively, indicating that the AUC increased non-proportionately with increasing doses.

Food does not affect the extent or rate of the absorption of verapamil from the controlled release verapamil hydrochloride sustained-release capsule. The verapamil hydrochloride sustained-release capsules 240 mg capsule when administered with food had a Cmax of 77 ng/mL which occurred 9.0 hours after dosing, and an AUC(O-inf) of 1387 ng∙hr/mL. Verapamil hydrochloride sustained-release capsules 240 mg under fasting conditions had a Cmax of 77 ng/mL which occurred 9.8 hours after dosing, and an AUC(O-inf) of 1541 ng∙hr/mL.

The bioequivalence of verapamil hydrochloride sustained-release capsule 240 mg, administered as the pellets sprinkled on applesauce and as the intact capsule, was demonstrated in a single-dose, cross-over study in 32 healthy adults. Comparative ratios (sprinkled/intact) of verapamil were 0.95, 1.02, and 1.01 for Cmax, Tmax, and AUC(O-inf) respectively. When the contents of the verapamil hydrochloride sustained-release capsule were administered by sprinkling onto one tablespoonful of applesauce, the rate and extent of verapamil absorption were found to be bioequivalent to the same dose when administered as an intact capsule. Similar results were observed with norverapamil.

The time to reach maximum verapamil concentrations (Tmax) with Verapamil Hydrochloride Sustained-Release Capsules has been found to be approximately 7-9 hours in each of the single dose (fasting), single dose (fed), the multiple dose (steady state) studies and dose proportionality pharmacokinetic studies. Similarly the apparent half-life (t1/2) has been found to be approximately 12 hours independent of dose. Aging may affect the pharmacokinetics of verapamil. Elimination half-life may be prolonged in the elderly.

In healthy man, orally administered verapamil HCl undergoes extensive metabolism in the liver. Twelve metabolites have been identified in plasma; all except norverapamil are present in trace amounts only. Norverapamil can reach steady-state plasma concentrations approximately equal to those of verapamil itself. The biologic activity of norverapamil appears to be approximately 20% that of verapamil.

Approximately 70% of an administered dose of verapamil HCl is excreted as metabolites in the urine and 16% or more in the feces within 5 days. About 3% to 4% is excreted in the urine as unchanged drug. Approximately 90% is bound to plasma proteins. In patients with hepatic insufficiency, metabolism is delayed and elimination half-life prolonged up to 14 to 16 hours (see PRECAUTIONS), the volume of distribution is increased and plasma clearance reduced to about 30% of normal. Verapamil clearance values suggest that patients with liver dysfunction may attain therapeutic verapamil plasma concentrations with one-third of the oral daily dose required for patients with normal liver function.

After four weeks of oral dosing (120 mg q.i.d.), verapamil and norverapamil levels were noted in the cerebrospinal fluid with estimated partition coefficient of 0.06 for verapamil and 0.04 for norverapamil.

In 10 healthy males, administration of oral verapamil (80 mg every 8 hours for 6 days) and a single oral dose of ethanol (0.8 g/kg), resulted in a 17% increase in mean peak ethanol concentrations (106.45 ± 21.40 to 124.23 ± 24.74 mg/dL) compared with placebo. (See PRECAUTIONS-Drug Interactions.)

The area under the blood ethanol concentration versus time curve (AUC over 12 hours) increased by 30% (365.67 ± 93.52 to 475.07 ± 97.24 mg∙hr/dL). Verapamil AUCs were positively correlated (r = 0.71) to increased ethanol blood AUC values.

Geriatric Use: The pharmacokinetics of verapamil GITS were studied after 5 consecutive nights of dosing 180 mg in 30 healthy young (19-43 years) versus 30 healthy elderly (65-80 years) male and female subjects. Older subjects had significantly higher mean verapamil Cmax, Cmin and AUC (0-24h) compared to younger subjects. Older subjects had mean AUCs that were approximately 1.7-2.0 times higher than those of younger subjects as well as a longer average verapamil t1/2 (approximately 20 hr vs 13 hr).

Hemodynamics and Myocardial Metabolism

Verapamil HCl reduces afterload and myocardial contractility. Improved left ventricular diastolic function in patients with IHSS and those with coronary heart disease has also been observed with verapamil HCl therapy. In most patients, including those with organic cardiac disease, the negative inotropic action of verapamil HCl is countered by reduction of afterload and cardiac index is usually not reduced. In patients with severe left ventricular dysfunction however, (e.g., pulmonary wedge pressure above 20 mm Hg or ejection fraction lower than 30%), or in patients on beta-adrenergic blocking agents or other cardio-depressant drugs, deterioration of ventricular function may occur. (See Drug Interactions.)

Pulmonary Function

Verapamil HCl does not induce broncho-constriction and hence, does not impair ventilatory function.

INDICATIONS AND USAGE

Verapamil hydrochloride sustained-release capsules are indicated for the treatment of hypertension, to lower blood pressure. Lowering blood pressure reduces the risk of fatal and nonfatal cardiovascular events, primarily strokes and myocardial infarctions. These benefits have been seen in controlled trials of antihypertensive drugs from a wide variety of pharmacologic classes including this drug.

Control of high blood pressure should be part of comprehensive cardiovascular risk management, including, as appropriate, lipid control, diabetes management, antithrombotic therapy, smoking cessation, exercise, and limited sodium intake. Many patients will require more than one drug to achieve blood pressure goals. For specific advice on goals and management, see published guidelines, such as those of the National High Blood Pressure Education Program's Joint National Committee on Prevention, Detection, Evaluation, and Treatment of High Blood Pressure (JNC).

Numerous antihypertensive drugs, from a variety of pharmacologic classes and with different mechanisms of action, have been shown in randomized controlled trials to reduce cardiovascular morbidity and mortality, and it can be concluded that it is blood pressure reduction, and not some other pharmacologic property of the drugs, that is largely responsible for those benefits. The largest and most consistent cardiovascular outcome benefit has been a reduction in the risk of stroke, but reductions in myocardial infarction and cardiovascular mortality also have been seen regularly.

Elevated systolic or diastolic pressure causes increased cardiovascular risk, and the absolute risk increase per mmHg is greater at higher blood pressures, so that even modest reductions of severe hypertension can provide substantial benefit. Relative risk reduction from blood pressure reduction is similar across populations with varying absolute risk, so the absolute benefit is greater in patients who are at higher risk independent of their hypertension (for example, patients with diabetes or hyperlipidemia), and such patients would be expected to benefit from more aggressive treatment to a lower blood pressure goal.

Some antihypertensive drugs have smaller blood pressure effects (as monotherapy) in black patients, and many antihypertensive drugs have additional approved indications and effects (e.g., on angina, heart failure, or diabetic kidney disease). These considerations may guide selection of therapy.

CONTRAINDICATIONS

Verapamil HCl is contraindicated in:

1. Severe left ventricular dysfunction. (See WARNINGS.)
2. Hypotension (less than 90 mm Hg systolic pressure) or cardiogenic shock.
3. Sick sinus syndrome (except in patients with a functioning artificial ventricular pacemaker).
4. Second- or third-degree AV block (except in patients with a functioning artificial ventricular pacemaker).
5. Patients with atrial flutter or atrial fibrillation and an accessory bypass tract (e.g., Wolff-Parkinson-White, Lown-Ganong-Levine syndromes). (See WARNINGS.)
6. Patients with known hypersensitivity to verapamil hydrochloride.

WARNINGS

Heart Failure

Verapamil has a negative inotropic effect which, in most patients, is compensated by its afterload reduction (decreased systemic vascular resistance) properties without a net impairment of ventricular performance. In clinical experience with 4,954 patients, 87 (1.8%) developed congestive heart failure or pulmonary edema. Verapamil should be avoided in patients with severe left ventricular dysfunction (e.g., ejection fraction less than 30% or moderate to severe symptoms of cardiac failure) and in patients with any degree of ventricular dysfunction if they are receiving a beta-adrenergic blocker. (See DRUG INTERACTIONS.) Patients with milder ventricular dysfunction should, if possible, be controlled with optimum doses of digitalis and/or diuretics before verapamil treatment (note interactions with digoxin under: PRECAUTIONS).

Hypotension

Occasionally, the pharmacologic action of verapamil may produce a decrease in blood pressure below normal levels which may result in dizziness or symptomatic hypotension. The incidence of hypotension observed in 4,954 patients enrolled in clinical trials was 2.5%. In hypertensive patients, decreases in blood pressure below normal are unusual. Tilt table testing (60 degrees) was not able to induce orthostatic hypotension.

Elevated Liver Enzymes

Elevations of transaminases with and without concomitant elevations in alkaline phosphatase and bilirubin have been reported. Such elevations have sometimes been transient and may disappear even in the face of continued verapamil treatment. Several cases of hepatocellular injury related to verapamil have been proven by rechallenge; half of these had clinical symptoms (malaise, fever, and/or right upper quadrant pain) in addition to elevations of SGOT, SGPT and alkaline phosphatase. Periodic monitoring of liver function in patients receiving verapamil is therefore prudent.

Accessory Bypass Tract (Wolff-Parkinson-White or Lown-Ganong-Levine)

Some patients with paroxysmal and/or chronic atrial flutter or atrial fibrillation and a coexisting accessory AV pathway have developed increased antegrade conduction across the accessory pathway bypassing the AV node, producing a very rapid ventricular response or ventricular fibrillation after receiving intravenous verapamil (or digitalis). Although a risk of this occurring with oral verapamil has not been established, such patients receiving oral verapamil may be at risk and its use in these patients is contraindicated. (See CONTRAINDICATIONS.)

Treatment is usually DC-cardioversion. Cardioversion has been used safely and effectively after oral verapamil.

Atrioventricular Block

The effect of verapamil on AV conduction and the SA node may lead to asymptomatic first-degree AV block and transient bradycardia, sometimes accompanied by nodal escape rhythms. PR interval prolongation is correlated with verapamil plasma concentrations, especially during the early titration phase of therapy. Higher degrees of AV block, however, were infrequently (0.8%) observed.

Marked first-degree block or progressive development to second- or third-degree AV block requires a reduction in dosage or, in rare instances, discontinuation of verapamil HCl and institution of appropriate therapy depending upon the clinical situation.

Patients with Hypertrophic Cardiomyopathy (IHSS)

In 120 patients with hypertrophic cardiomyopathy (most of them refractory or intolerant to propranolol) who received therapy with verapamil at doses up to 720 mg/day, a variety of serious adverse effects were seen. Three patients died in pulmonary edema; all had severe left ventricular outflow obstruction and a past history of left ventricular dysfunction. Eight other patients had pulmonary edema and/or severe hypotension; abnormally high (over 20 mm Hg) capillary wedge pressure and a marked left ventricular outflow obstruction were present in most of these patients. Concomitant administration of quinidine (see Drug Interactions) preceded the severe hypotension in 3 of the 8 patients (2 of whom developed pulmonary edema). Sinus bradycardia occurred in 11% of the patients, second-degree AV block in 4% and sinus arrest in 2%. It must be appreciated that this group of patients had a serious disease with a high mortality rate. Most adverse effects responded well to dose reduction and only rarely did verapamil have to be discontinued.

PRECAUTIONS

THE CONTENTS OF THE VERAPAMIL HYDROCHLORIDE SUSTAINED-RELEASE CAPSULES SHOULD NOT BE CRUSHED OR CHEWED. VERAPAMIL HYDROCHLORIDE SUSTAINED-RELEASE CAPSULES ARE TO BE SWALLOWED WHOLE OR THE ENTIRE CONTENTS OF THE CAPSULE SPRINKLED ONTO APPLESAUCE (see DOSAGE AND ADMINISTRATION).

General

Use in Patients with Impaired Hepatic Function
Since verapamil is highly metabolized by the liver, it should be administered cautiously to patients with impaired hepatic function. Severe liver dysfunction prolongs the elimination half-life of immediate-release verapamil to about 14 to 16 hours; hence, approximately 30% of the dose given to patients with normal liver function should be administered to these patients. Careful monitoring for abnormal prolongation of the PR interval or other signs of excessive pharmacologic effects (see OVERDOSAGE) should be carried out.

Use in Patients with Attenuated (Decreased) Neuromuscular Transmission
It has been reported that verapamil decreases neuromuscular transmission in patients with Duchenne's muscular dystrophy, and that verapamil prolongs recovery from the neuromuscular blocking agent vecuronium and causes a worsening of myasthenia gravis. It may be necessary to decrease the dosage of verapamil when it is administered to patients with attenuated neuromuscular transmission.

Use in Patients with Impaired Renal Function
About 70% of an administered dose of verapamil is excreted as metabolites in the urine. Until further data are available, verapamil should be administered cautiously to patients with impaired renal function. These patients should be carefully monitored for abnormal prolongation of the PR interval or other signs of overdosage. (See OVERDOSAGE.)

Information for Patients

When the sprinkle method of administration is prescribed, details of the proper technique should be explained to the patient. (See DOSAGE AND ADMINISTRATION.)

Drug-Drug Interactions

Drug Interactions: Effects of other drugs on verapamil pharmacokinetics

In vitro metabolic studies indicate that verapamil is metabolized by cytochrome P450, CYP3A4, CYP1A2, and CYP2C. Clinically significant interactions have been reported with inhibitors of CYP3A4 (e.g., erythromycin, ritonavir) causing elevation of plasma levels of verapamil while inducers of CYP3A4 (e.g., rifampin) have caused a lowering of plasma levels of verapamil. Hypotension, bradyarrhythmias, and lactic acidosis have been observed in patients receiving concurrent telithromycin, an antibiotic in the ketolide class of antibiotics.

Ivabradine

Concurrent use of verapamil increases exposure to ivabradine and may exacerbate bradycardia and conductions disturbances. Avoid concomitant use of ivabradine and verapamil.

HMG-CoA Reductase Inhibitors

The use of HMG-CoA reductase inhibitors that are CYP3A4 substrates in combination with verapamil has been associated with reports of myopathy/rhabdomyolysis.

Co-administration of multiple doses of 10 mg of verapamil with 80 mg simvastatin resulted in exposure to simvastatin 2.5-fold that following simvastatin alone. Limit the dose of simvastatin in patients on verapamil to 10 mg daily. Limit the daily dose of lovastatin to 40 mg. Lower starting and maintenance doses of other CYP3A4 substrates (e.g., atorvastatin) may be required as verapamil may increase the plasma concentration of these drugs.

Beta Blockers

Concomitant therapy with beta-adrenergic blockers and verapamil may result in additive negative effects on heart rate, atrioventricular conduction, and/or cardiac contractility. The combination of sustained-release verapamil and beta-adrenergic blocking agents has not been studied. However, there have been reports of excess bradycardia and AV block, including complete heart block, when the combination has been used for the treatment of hypertension.

For hypertensive patients, the risk of combined therapy may outweigh the potential benefits. The combination should be used only with caution and close monitoring.

Asymptomatic bradycardia (36 beats/min) with a wandering atrial pacemaker has been observed in a patient receiving concomitant timolol (a beta-adrenergic blocker) eyedrops and oral verapamil.

A decrease in metoprolol clearance has been reported when verapamil and metoprolol were administered together. A similar effect has not been observed when verapamil and atenolol are given together.

Clonidine

Sinus bradycardia resulting in hospitalization and pacemaker insertion has been reported in association with the use of clonidine concurrently with verapamil. Monitor heart rate in patients receiving concomitant verapamil and clonidine.

Digitalis

Consider reducing digoxin dose when verapamil and digoxin are to be given together. Monitor digoxin level periodically during therapy. Chronic verapamil treatment can increase serum digoxin levels by 50% to 75% during the first week of therapy, and this can result in digitalis toxicity. In patients with hepatic cirrhosis the influence of verapamil on digoxin pharmacokinetics is magnified. Verapamil may reduce total body clearance and extrarenal clearance of digoxin by 27% and 29%, respectively. If digoxin toxicity is suspected, suspend or discontinue digoxin therapy.

In previous clinical trials with other verapamil formulations related to the control of ventricular response in patients taking digoxin who had atrial fibrillation or atrial flutter, ventricular rates below 50/min at rest occurred in 15% of patients, and asymptomatic hypotension occurred in 5% of patients.

Antihypertensive Agents

Verapamil administered concomitantly with oral antihypertensive agents (e.g., vasodilators, angiotensin-converting enzyme inhibitors, diuretics, beta blockers) will usually have an additive effect on lowering blood pressure. Patients receiving these combinations should be appropriately monitored. Concomitant use of agents that attenuate alpha-adrenergic function with verapamil may result in reduction in blood pressure that is excessive in some patients. Such an effect was observed in one study following the concomitant administration of verapamil and prazosin.

Antiarrhythmic Agents

Disopyramide: Until data on possible interactions between verapamil and disopyramide phosphate are obtained, disopyramide should not be administered within 48 hours before or 24 hours after verapamil administration.

Flecainide: A study in healthy volunteers showed that the concomitant administration of flecainide and verapamil may have additive effects on myocardial contractility, AV conduction, and repolarization. Concomitant therapy with flecainide and verapamil may result in additive negative inotropic effect and prolongation of atrioventricular conduction.

Quinidine: In a small number of patients with hypertrophic cardiomyopathy (IHSS), concomitant use of verapamil and quinidine resulted in significant hypotension. Until further data are obtained, combined therapy of verapamil and quinidine in patients with hypertrophic cardiomyopathy should probably be avoided.
The electrophysiological effects of quinidine and verapamil on AV conduction were studied in 8 patients. Verapamil significantly counteracted the effects of quinidine on AV conduction. There has been a report of increased quinidine levels during verapamil therapy.

Nitrates: Verapamil has been given concomitantly with short- and long-acting nitrates without any undesirable drug interactions. The pharmacologic profile of both drugs and the clinical experience suggest beneficial interactions.

Alcohol: Verapamil has been found to significantly inhibit ethanol elimination resulting in elevated blood ethanol concentrations that may prolong the intoxicating effects of alcohol. (See CLINICAL PHARMACOLOGY - Pharmacokinetics and Metabolism.)

Other

Aspirin: In a few reported cases, coadministration of verapamil with aspirin has led to increased bleeding times greater than observed with aspirin alone.

Cimetidine: The interaction between cimetidine and chronically administered verapamil has not been studied. Variable results on clearance have been obtained in acute studies of healthy volunteers; clearance of verapamil was either reduced or unchanged.

Grapefruit Juice: Grapefruit juice may significantly increase concentrations of verapamil. Grapefruit juice given to nine healthy volunteers increased S- and R- verapamil AUC0-12 by 36% and 28%, respectively. Steady state Cmax and Cmin of S-verapamil increased by 57% and 16.7%, respectively with grapefruit juice compared to control. Similarly, Cmax and Cmin of R-verapamil increased by 40% and 13%, respectively. Grapefruit juice did not affect half-life, nor was there a significant change in AUC0-12 ratio R/S compared to control. Grapefruit juice did not cause a significant difference in the PK of norverapamil. This increase in verapamil plasma concentration is not expected to have any clinical consequences.

Lithium: Pharmacokinetic and pharmacodynamic interactions between oral verapamil and lithium have been reported. The former may result in a lowering of serum lithium levels in patients receiving chronic stable oral lithium therapy. The latter may result in an increased sensitivity to the effects of lithium. Patients receiving both drugs must be monitored carefully.

Carbamazepine: Verapamil therapy may increase carbamazepine concentrations during combined therapy. This may produce carbamazepine side effects such as diplopia, headache, ataxia, or dizziness.

Rifampin: Therapy with rifampin may markedly reduce oral verapamil bioavailability.

Phenobarbital: Phenobarbital therapy may increase verapamil clearance.

Cyclosporine: Verapamil therapy may increase serum levels of cyclosporine.

Theophylline: Verapamil may inhibit the clearance and increase the plasma levels of theophylline.

Inhalation Anesthetics: Animal experiments have shown that inhalation anesthetics depress cardiovascular activity by decreasing the inward movement of calcium ions. When used concomitantly, inhalation anesthetics and calcium antagonists, such as verapamil, should be titrated carefully to avoid excessive cardiovascular depression.

Neuromuscular Blocking Agents: Clinical data and animal studies suggest that verapamil may potentiate the activity of neuromuscular blocking agents (curare-like and depolarizing). It may be necessary to decrease the dose of verapamil and/or the dose of the neuromuscular blocking agent when the drugs are used concomitantly.

Mammalian target of rapamycin (mTOR) inhibitors

In a study of 25 healthy volunteers with co-administration of verapamil with sirolimus, whole blood sirolimus Cmax and AUC were increased 130% and 120%, respectively. Plasma S (-) verapamil Cmax and AUC were both increased 50%. Co-administration of verapamil with everolimus in 16 healthy volunteers increased the Cmax and AUC of everolimus by 130% and 250%, respectively. With concomitant use of mTOR inhibitors (e.g., sirolimus, temsirolimus, and everolimus) and verapamil, consider appropriate dose reductions of both medications.

Carcinogenesis, Mutagenesis, Impairment of Fertility

An 18-month toxicity study in rats, at a low multiple (6 fold) of the maximum recommended human dose, and not the maximum tolerated dose, did not suggest a tumorigenic potential. There was no evidence of a carcinogenic potential of verapamil administered in the diet of rats for two years at doses of 10, 35 and 120 mg/kg per day or approximately 1x, 3.5x and 12x, respectively, the maximum recommended human daily dose (480 mg per day or 9.6 mg/kg/day).

Verapamil was not mutagenic in the Ames test in 5 test strains at 3 mg per plate, with or without metabolic activation.

Studies in female rats at daily dietary doses up to 5.5 times (55 mg/kg/day) the maximum recommended human dose did not show impaired fertility. Effects on male fertility have not been determined.

Pregnancy

Pregnancy Category C. Reproduction studies have been performed in rabbits and rats at oral doses up to 1.5 (15 mg/kg/day) and 6 (60 mg/kg/day) times the maximum recommended human daily dose, respectively, and have revealed no evidence of teratogenicity. In the rat, however, this multiple of the human dose was embryocidal and retarded fetal growth and development, probably because of adverse maternal effects reflected in reduced weight gains of the dams. This oral dose has also been shown to cause hypotension in rats. There are no adequate and well-controlled studies in pregnant women. Because animal reproduction studies are not always predictive of human response, this drug should be used during pregnancy only if clearly needed. Verapamil crosses the placental barrier and can be detected in umbilical vein blood at delivery.

Labor and Delivery

It is not known whether the use of verapamil during labor or delivery has immediate or delayed adverse effects on the fetus, or whether it prolongs the duration of labor or increases the need for forceps delivery or other obstetric intervention. Such adverse experiences have not been reported in the literature, despite a long history of use of verapamil HCl in Europe in the treatment of cardiac side effects of beta-adrenergic agonist agents used to treat premature labor.

Nursing Mothers

Verapamil is excreted in human milk. Because of the potential for adverse reactions in nursing infants from verapamil, nursing should be discontinued while verapamil is administered.

Pediatric Use

Safety and efficacy of verapamil in children below the age of 18 years have not been established.

Geriatric Use

Clinical studies of verapamil did not include sufficient numbers of subjects aged 65 and over to determine whether they respond differently from younger subjects. Other reported clinical experience has not identified differences in responses between the elderly and younger patients. In general, dose selection for an elderly patient should be cautious, usually starting at the low end of the dosing range, reflecting the greater frequency of decreased hepatic, renal, or cardiac function, and of concomitant disease or other drug therapy.

Aging may affect the pharmacokinetics of verapamil. Elimination half-life may be prolonged in the elderly (see CLINICAL PHARMACOLOGY, Pharmacokinetics and Metabolism).

Verapamil is highly metabolized by the liver, and about 70% of the administered dose is excreted as metabolites in the urine. Clinical circumstances, some of which may be more common in the elderly, such as hepatic or renal impairment, should be considered (see PRECAUTIONS, General). In general, lower initial doses of verapamil hydrochloride sustained-release capsules may be warranted in the elderly (see DOSAGE AND ADMINISTRATION).

Animal Pharmacology and/or Animal Toxicology

In chronic animal toxicology studies verapamil caused lenticular and/or suture line changes at 30 mg/kg/day or greater and frank cataracts at 62.5 mg/kg/day or greater in the beagle dog but not the rat. Development of cataracts due to verapamil has not been reported in man.

ADVERSE REACTIONS

Serious adverse reactions are uncommon when verapamil HCl therapy is initiated with upward dose titration within the recommended single and total daily dose. See WARNINGS for discussion of heart failure, hypotension, elevated liver enzymes, AV block, and rapid ventricular response. Reversible (upon discontinuation of verapamil) non-obstructive, paralytic ileus has been infrequently reported in association with the use of verapamil.

In clinical trials involving 285 hypertensive patients on verapamil hydrochloride sustained-release capsules for greater than 1 week the following adverse reactions were reported in greater than 1.0% of the patients:

Constipation | 7.4%
Headache | 5.3%
Dizziness | 4.2%
Lethargy | 3.2%
Dyspepsia | 2.5%
Rash | 1.4%
Ankle Edema | 1.4%
Sleep Disturbance | 1.4%
Myalgia | 1.1%

In clinical trials of other formulations of verapamil HCl (N=4,954) the following reactions have occurred at rates greater than 1.0%:

Constipation | 7.3%
Dizziness | 3.3%
Nausea | 2.7%
Hypotension | 2.5%
Edema | 1.9%
Headache | 2.2%
Rash | 1.2%
CHF/Pulmonary Edema | 1.8%
Fatigue | 1.7%
Bradycardia (HR<50/min) | 1.4%
AV block-total 1°, 2°, 3° | 1.2%
2° and 3° | 0.8%
Flushing | 0.6%
Elevated Liver Enzymes (See WARNINGS)

In clinical trials related to the control of ventricular response in digitalized patients who had atrial fibrillation or atrial flutter, ventricular rate below 50/min at rest occurred in 15% of patients and asymptomatic hypotension occurred in 5% of patients.

The following reactions, reported in 1.0% or less of patients, occurred under conditions (open trials, marketing experience) where a causal relationship is uncertain; they are listed to alert the physician to a possible relationship:

Cardiovascular: angina pectoris, atrioventricular dissociation, chest pain, claudication, myocardial infarction, palpitations, purpura (vasculitis), syncope.

Digestive System: diarrhea, dry mouth, gastrointestinal distress, gingival hyperplasia.

Hemic and Lymphatic: ecchymosis or bruising.

Nervous System: cerebrovascular accident, confusion, equilibrium disorders, extrapyramidal symptoms, insomnia, muscle cramps, paresthesia, psychotic symptoms, shakiness, somnolence.

Respiratory: dyspnea.

Skin: arthralgia and rash, exanthema, hair loss, hyperkeratosis, maculae, sweating, urticaria, Stevens-Johnson syndrome, erythema multiforme.

Special Senses: blurred vision, tinnitus.

Urogenital: gynecomastia, impotence, increased urination, spotty menstruation.

Treatment of Acute Cardiovascular Adverse Reactions

The frequency of cardiovascular adverse reactions which require therapy is rare; hence, experience with their treatment is limited. Whenever severe hypotension or complete AV block occurs following oral administration of verapamil, the appropriate emergency measures should be applied immediately, e.g., intravenously administered isoproterenol HCl, levarterenol bitartrate, atropine (all in the usual doses), or calcium gluconate (10% solution). In patients with hypertrophic cardiomyopathy (IHSS), alpha-adrenergic agents (phenylephrine, metaraminol bitartrate or methoxamine) should be used to maintain blood pressure, and isoproterenol and levarterenol should be avoided. If further support is necessary, inotropic agents (dopamine or dobutamine) may be administered. Actual treatment and dosage should depend on the severity and the clinical situation and the judgment and experience of the treating physician.

To report SUSPECTED ADVERSE EVENTS, contact Actavis at 1-800-272-5525 or FDA at 1-800-FDA-1088 or http://www.fda.gov/ for voluntary reporting of adverse reactions.

OVERDOSAGE

There is no specific antidote for verapamil overdosage; treatment should be supportive. Delayed pharmacodynamic consequences may occur with sustained-release formulations, and patients should be observed for at least 48 hours, preferably under continuous hospital care. Reported effects include hypotension, bradycardia, cardiac conduction defects, arrhythmias, hyperglycemia, and decreased mental status. In addition, there have been literature reports of non-cardiogenic pulmonary edema in patients taking large overdoses of verapamil (up to approximately 9g).

In acute overdosage, gastrointestinal decontamination with cathartics and whole bowel irrigation should be considered. Calcium, inotropes (i.e., isoproterenol, dopamine, and glucagon), atropine, vasopressors (i.e., norepinephrine, and epinephrine), and cardiac pacing have been used with variable results to reverse hypotension and myocardial depression. In a few reported cases, overdose with calcium channel blockers that was initially refractory to atropine became more responsive to this treatment when the patients received large doses (close to 1g/hour for more than 24 hours) of calcium chloride. Calcium chloride is preferred to calcium gluconate since it provides 3 times more calcium per volume. Asystole should be handled by the usual measures including cardiopulmonary resuscitation. Verapamil cannot be removed by hemodialysis.

DOSAGE AND ADMINISTRATION

Essential Hypertension

The dose of verapamil hydrochloride sustained-release capsules should be individualized by titration. The usual daily dose of sustained-release verapamil, verapamil hydrochloride sustained-release capsules, in clinical trials has been 240 mg given by mouth once daily in the morning. However, initial doses of 120 mg a day may be warranted in patients who may have an increased response to verapamil (e.g., elderly, small people, etc.). Upward titration should be based on therapeutic efficacy and safety evaluated approximately 24 hours after dosing. The antihypertensive effects of verapamil hydrochloride sustained-release capsules are evident within the first week of therapy.

If adequate response is not obtained with 120 mg of verapamil hydrochloride sustained-release capsules, the dose may be titrated upward in the following manner:

(a) 180 mg in the morning.

(b) 240 mg in the morning.

(c) 360 mg in the morning.

(d) 480 mg in the morning.

Verapamil hydrochloride sustained-release capsules are for once-a-day administration. When switching from immediate-release verapamil to verapamil hydrochloride sustained-release capsules, the same total daily dose of verapamil hydrochloride sustained-release capsules can be used.

As with immediate-release verapamil, dosages of verapamil hydrochloride sustained-release capsules should be individualized and titration may be needed in some patients.

Sprinkling the Capsule Contents on Food

Verapamil hydrochloride sustained-release capsules may also be administered by carefully opening the capsule and sprinkling the pellets on a spoonful of applesauce. The applesauce should be swallowed immediately without chewing and followed with a glass of cool water to ensure complete swallowing of the pellets. The applesauce used should not be hot, and it should be soft enough to be swallowed without chewing. Any pellet/applesauce mixture should be used immediately and not stored for future use. Subdividing the contents of a verapamil hydrochloride sustained-release capsule is not recommended.

HOW SUPPLIED

Verapamil hydrochloride sustained-release capsules are supplied in four dosage strengths:

360 mg - | Two-piece, size 00 hard gelatin capsule (lavender cap/yellow body), printed with 60274 and 360 mg in black ink, supplied as follows:
 | NDC 63629-8842-1 - Bottle of 100s

Store at Controlled Room Temperature 20° to 25°C (68° to 77°F). [See USP]. Avoid excessive heat. Brief digressions above 25°C, while not detrimental, should be avoided. Protect from moisture. Dispense in tight, light-resistant container as defined in USP.

Repackaged/Relabeled by:
Bryant Ranch Prepack, Inc.
Burbank, CA 91504

Rx only

Manufactured by:

Recro® Gainesville LLC
Gainesville, GA 30504

6002451-03

Revised: October 2019

Distributed by:
Actavis Pharma, Inc.
Parsippany, NJ 07054 USA

PACKAGE LABEL

Verapamil Hydrochloride Sustained-Release 360mg Capsules